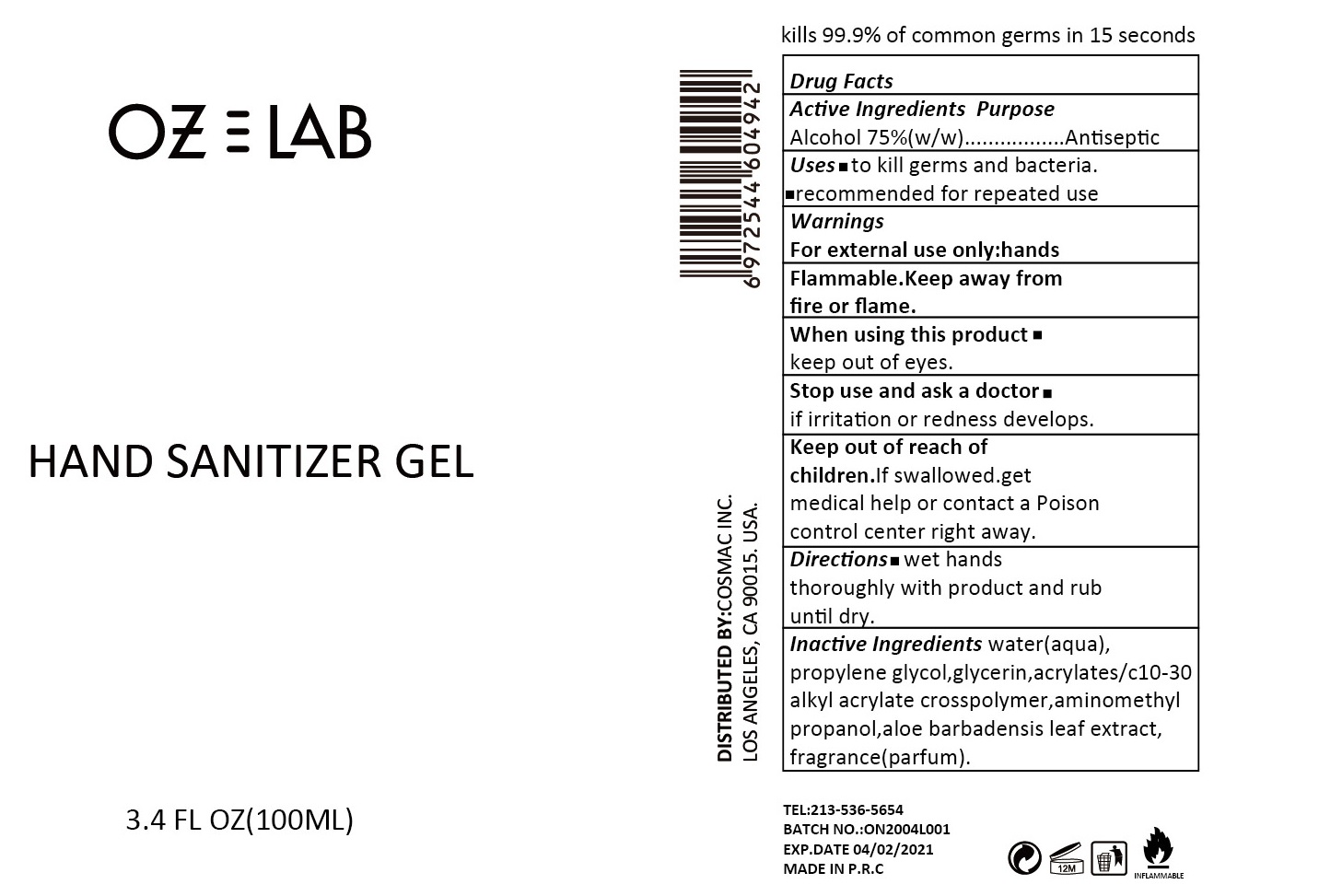 DRUG LABEL: OZLAB Hand Sanitizer
NDC: 75531-006 | Form: GEL
Manufacturer: Zhejiang Ounuo Cosmetics Co., Ltd.
Category: otc | Type: HUMAN OTC DRUG LABEL
Date: 20200617

ACTIVE INGREDIENTS: alcohol 75 mL/100 mL
INACTIVE INGREDIENTS: WATER; PROPYLENE GLYCOL; CARBOMER 934; GLYCERIN; CARBOMER COPOLYMER TYPE A; AMINOMETHYLPROPANOL; ALOE VERA LEAF

Drug facts

Active ingredient Purpose

Alcohol 75% (w/w) ... Antiseptic

PURPOSE

- to kill germs and bacteria.
- recommended for repeated use.

KEEP OUT OF REACH OF CHILDREN

If swallowed, get medical help or contact a Poison Control Center right away.

INDICATIONS AND USAGE

keep out of eyes

WARNINGS

For external use only: hands
Flammable. Keep away from fire or flame.

When using this products, keep out of eyes.

Stop using and ask a doctor, if irritation or redness develops.

DOSAGE AND ADMINISTRATION

- Wet hands thoroughly with product andd rub until dry.

INACTIVE INGREDIENT

Water (aqua), propylene glycol, Glycerin, acrylates/c10-30 alkyl acrylate crosspolymer, aminomethyl Propanol, aloe barbadensis leaf extract, fragrance (parfum)